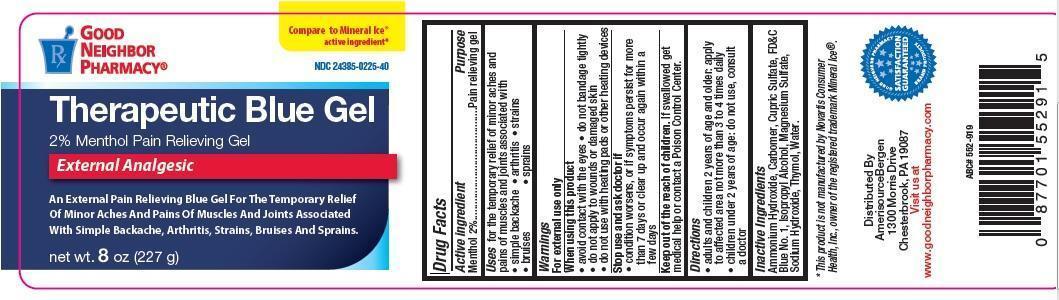 DRUG LABEL: Good Neighbor Pharmacy Therapeutic Blue
NDC: 24385-225 | Form: GEL
Manufacturer: AmerisourceBergen Drug Corporation
Category: otc | Type: HUMAN OTC DRUG LABEL
Date: 20150722

ACTIVE INGREDIENTS: MENTHOL 2 g/100 g
INACTIVE INGREDIENTS: AMMONIA; CARBOMER 934; CUPRIC SULFATE; FD&C BLUE NO. 1; ISOPROPYL ALCOHOL; MAGNESIUM SULFATE; SODIUM HYDROXIDE; THYMOL; WATER

Good Neighbor Pharmacy Therapeutic Blue

Drug Facts

Active Ingredients

Active ingredient

Menthol 2%

PURPOSE

pain relieving gel

Uses

for the temporary relief of minor aches and

pains of muscles and joints associated with

• simple backache • arthritis • strains

• bruises • sprains

warnings

For external use only

when using this product

• avoid contact with the eyes

• do not bandage tightly

• do not apply to wounds or damaged skin

• do not use with heating pads or other heating devices

Stop using and ask a doctor if

• condition worsens, or if symptoms persist for more

than 7 days or clear up and occur again within a

few days

Keep out of the reach of children

If swallowed get medical help or contact a Poison Control Center.

Directions

• adults and children 2 years of age and older: apply

to affected area not more than 3 to 4 times daily

• children under 2 years of age: do not use, consult a doctor

Inactive Ingredients

Ammonium Hydroxide, Carbomer, Cupric Sulfate, FD&C Blue No. 1,

Isopropyl Alcohol, Magnesium Sulfate,

Sodium Hydroxide, Thymol, Water.

This product is not manufactured by Novartis Consumer

Health, Inc., owner of the registered trademark Mineral Ice®.